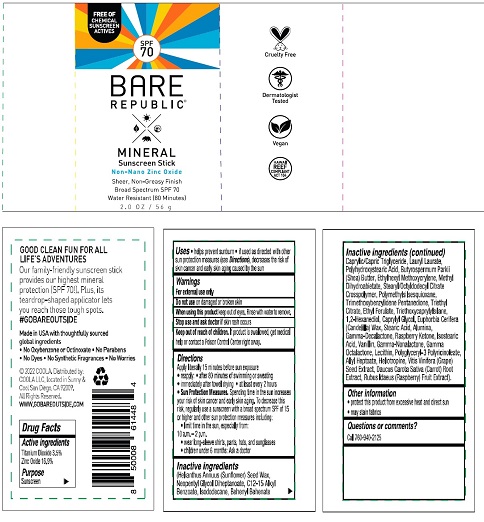 DRUG LABEL: Bare Republic Big Adventure Stick SPF 70
NDC: 79753-026 | Form: STICK
Manufacturer: COOLA
Category: otc | Type: HUMAN OTC DRUG LABEL
Date: 20231220

ACTIVE INGREDIENTS: TITANIUM DIOXIDE 3.5 g/100 g; ZINC OXIDE 16.9 g/100 g
INACTIVE INGREDIENTS: HELIANTHUS ANNUUS SEED WAX; NEOPENTYL GLYCOL DIHEPTANOATE; ALKYL (C12-15) BENZOATE; ISODODECANE; BEHENYL BEHENATE; MEDIUM-CHAIN TRIGLYCERIDES; LAURYL LAURATE; POLYHYDROXYSTEARIC ACID (2300 MW); SHEA BUTTER; ETHYLHEXYL METHOXYCRYLENE; METHYL DIHYDROABIETATE; STEARYL/OCTYLDODECYL CITRATE CROSSPOLYMER; POLYMETHYLSILSESQUIOXANE (11 MICRONS); TRIMETHOXYBENZYLIDENE PENTANEDIONE; TRIETHYL CITRATE; ETHYL FERULATE; TRIETHOXYCAPRYLYLSILANE; 1,2-HEXANEDIOL; CAPRYLYL GLYCOL; CANDELILLA WAX; STEARIC ACID; ALUMINUM OXIDE; .GAMMA.-DECALACTONE; 4-(P-HYDROXYPHENYL)-2-BUTANONE; ISOSTEARIC ACID; VANILLIN; .GAMMA.-NONALACTONE; .GAMMA.-OCTALACTONE; LECITHIN, SUNFLOWER; POLYGLYCERYL-3 PENTARICINOLEATE; ALLYL HEPTANOATE; PIPERONAL; VITIS VINIFERA SEED; CARROT; RASPBERRY

Bare Republic Mineral Sunscreen Stick SPF 70

DRUG FACTS

Active Ingredients
Titanium Dioxide 3.5% Zinc Oxide 16.9%

Purpose
Sunscreen

INDICATIONS AND USAGE

Uses • helps prevent sunburn • if used as directed with other
sun protection measures(see Directions) decreases the risk of
skin cancer and early skin aging caused by the sun

Warnings
For external use only

Do not use on damaged or broken skin

When using this product keep out of eyes.
Rinse with water to remove.

Stop use and ask doctor if skin rash occurs

Keep out of reach of children. If product is swallowed
get medical help or contact a Poison Control Center right away.

Directions
Apply liberally 15 minutes before sun exposure
• reapply: • after 80 minutes swimming or sweating
• immediately after towel drying • at least every 2 hours
• Sun Protection Measures. Spending time in the sun increases
your risk of skin cancer and early skin aging. To decrease this
risk, regularly use a sunscreen with a broad spectrum SPF of 15
or higher and after sun protection measures including:
• limit time in the sun, especially from 10 a.m. – 2 p.m.
• wear long-sleeve shirts, pants, hats, and sunglasses.
• children under 6 months: Ask a doctor

Inactive Ingredients

Helianthus Annuus (Sunflower) Seed Wax,
Neopentyl Glycol Diheptanoate, C12-15 Alkyl
Benzoate, Isododecane, Behenyl Behenate,
Caprylic/Capric Triglyceride, Lauryl Laurate,
Polyhydroxystearic Acid, Butyrospermum Parkii
(Shea) Butter, Ethylhexyl Methoxycrylene, Methyl
Dihydroabietate, Stearyl/Octyldodecyl Citrate
Crosspolymer, Polymethylsilsesquioxane,
Trimethoxybenzylidene Pentanedione, Triethyl
Citrate, Ethyl Ferulate, Triethoxycaprylylsilane,
1,2-Hexanediol, Caprylyl Glycol, Euphorbia Cerifera
(Candelilla) Wax, Stearic Acid, Alumina,
Gamma-Decalactone, Raspberry Ketone, Isostearic
Acid, Vanillin, Gamma-Nonalactone, Gamma
Octalactone, Lecithin, Polyglyceryl-3 Polyricinoleate,
Allyl Heptoate, Heliotropine, Vitis Vinifera (Grape)
Seed Extract, Daucus Carota Sativa (Carrot) Root
Extract, Rubus Idaeus (Raspberry) Fruit Extract.

Other Information

- protect this product from excessive heat and direct sun
- may stain fabrics

Questions or Comments? Call 760-940-2125

Package for BARE REPUBLIC MINERAL Sunscreen Stick

SPF 70

BARE

REPUBLIC ®

MINERAL

Sunscreen Stick

2.0 OZ / 56 g

Distributed by:

COOLA LLC, Located in Sunny &

Cool San Diego, CA 92009.

WWW.GOBAREOUTSIDE.COM

res